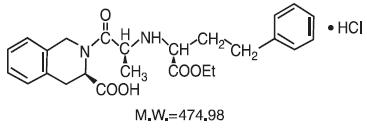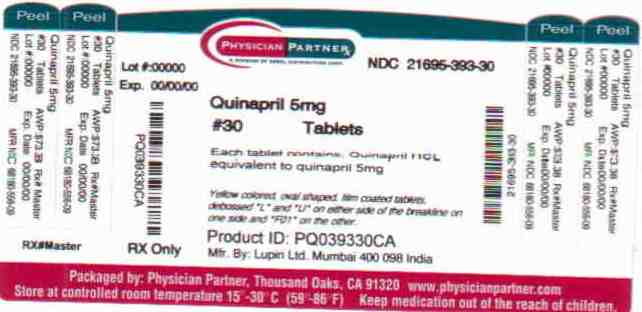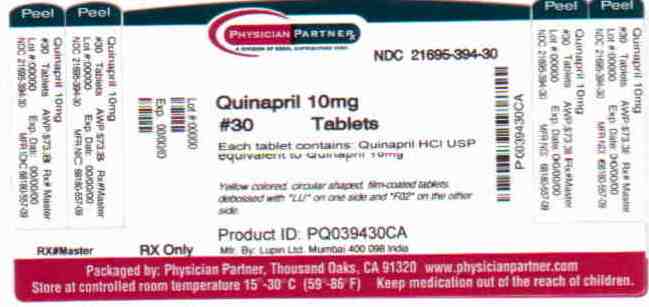 DRUG LABEL: Quinapril
NDC: 21695-393 | Form: TABLET
Manufacturer: Rebel Distributors Corp
Category: prescription | Type: HUMAN PRESCRIPTION DRUG LABEL
Date: 20110104

ACTIVE INGREDIENTS: QUINAPRIL HYDROCHLORIDE 5 mg/1 1
INACTIVE INGREDIENTS: CROSPOVIDONE; FERRIC OXIDE YELLOW; MAGNESIUM CARBONATE; MAGNESIUM STEARATE; CELLULOSE, MICROCRYSTALLINE; POLYVINYL ALCOHOL; POVIDONE; TALC; TITANIUM DIOXIDE; XANTHAN GUM; LECITHIN, SOYBEAN

QUINAPRIL TABLETS USP
5 mg, 10 mg, 20 mg and 40 mg

Rx only

BOXED WARNING

USE IN PREGNANCY

When used in pregnancy during the second and third trimesters, ACE inhibitors can cause injury and even death to the developing fetus. When pregnancy is detected, quinapril tablets should be discontinued as soon as possible. See WARNINGS, Fetal/Neonatal Morbidity and Mortality.

DESCRIPTION

Quinapril tablets (quinapril hydrochloride) is the hydrochloride salt of quinapril, the ethyl ester of a non-sulfhydryl, angiotensin-converting enzyme (ACE) inhibitor, quinaprilat.

Quinapril hydrochloride is chemically described as [3S-[2[R*(R*)], 3R*]]-2-[2-[[1- (ethoxycarbonyl)-3-phenylpropyl]amino]-1-oxopropyl]-1,2,3,4-tetrahydro-3- isoquinolinecarboxylic acid, monohydrochloride. Its empirical formula is C25H30N2O5 •HCl and its structural formula is:

Quinapril hydrochloride is a white to off-white amorphous powder that is freely soluble in aqueous solvents.

Quinapril tablets contain 5 mg, 10 mg, 20 mg, or 40 mg of quinapril for oral administration. Each film-coated tablet also contains crospovidone, iron oxide yellow, lecithin, magnesium carbonate, magnesium stearate, microcrystalline cellulose, polyvinyl alcohol, povidone, talc, titanium dioxide and xanthan gum.

CLINICAL PHARMACOLOGY

Mechanism of Action:

Quinapril is deesterified to the principal metabolite, quinaprilat, which is an inhibitor of ACE activity in human subjects and animals. ACE is a peptidyl dipeptidase that catalyzes the conversion of angiotensin I to the vasoconstrictor, angiotensin II. The effect of quinapril in hypertension appears to result primarily from the inhibition of circulating and tissue ACE activity, thereby reducing angiotensin II formation. Quinapril inhibits the elevation in blood pressure caused by intravenously administered angiotensin I, but has no effect on the pressor response to angiotensin II, norepinephrine or epinephrine. Angiotensin II also stimulates the secretion of aldosterone from the adrenal cortex, thereby facilitating renal sodium and fluid reabsorption. Reduced aldosterone secretion by quinapril may result in a small increase in serum potassium. In controlled hypertension trials, treatment with quinapril alone resulted in mean increases in potassium of 0.07 mmol/L (see PRECAUTIONS). Removal of angiotensin II negative feedback on renin secretion leads to increased plasma renin activity (PRA).

While the principal mechanism of antihypertensive effect is thought to be through the rennin-angiotensin-aldosterone system, quinapril exerts antihypertensive actions even in patients with low renin hypertension. Quinapril was an effective antihypertensive in all races studied, although it was somewhat less effective in blacks (usually a predominantly low renin group) than in nonblacks. ACE is identical to kininase II, an enzyme that degrades bradykinin, a potent peptide vasodilator; whether increased levels of bradykinin play a role in the therapeutic effect of quinapril remains to be elucidated.

Pharmacokinetics and Metabolism:

Following oral administration, peak plasma quinapril concentrations are observed within one hour. Based on recovery of quinapril and its metabolites in urine, the extent of absorption is at least 60%. The rate and extent of quinapril absorption are diminished moderately (approximately 25-30%) when quinapril tablets are administered during a high-fat meal. Following absorption, quinapril is deesterified to its major active metabolite, quinaprilat (about 38% of oral dose), and to other minor inactive metabolites. Following multiple oral dosing of quinapril, there is an effective accumulation half-life of quinaprilat of approximately 3 hours, and peak plasma quinaprilat concentrations are observed approximately 2 hours post-dose. Quinaprilat is eliminated primarily by renal excretion, up to 96% of an IV dose, and has an elimination half-life in plasma of approximately 2 hours and a prolonged terminal phase with a half-life of 25 hours. The pharmacokinetics of quinapril and quinaprilat are linear over a single-dose range of 5-80 mg doses and 40-160 mg in multiple daily doses. Approximately 97% of either quinapril or quinaprilat circulating in plasma is bound to proteins.

In patients with renal insufficiency, the elimination half-life of quinaprilat increases as creatinine clearance decreases. There is a linear correlation between plasma quinaprilat clearance and creatinine clearance. In patients with end-stage renal disease, chronic hemodialysis or continuous ambulatory peritoneal dialysis has little effect on the elimination of quinapril and quinaprilat. Elimination of quinaprilat may be reduced in elderly patients (≥65 years); this reduction is attributable to decrease in renal function (see DOSAGE AND ADMINISTRATION). Quinaprilat concentrations are reduced in patients with alcoholic cirrhosis due to impaired deesterification of quinapril. Studies in rats indicate that quinapril and its metabolites do not cross the blood-brain barrier.

Pharmacodynamics and Clinical Effects:

Hypertension:

Single doses of 20 mg of quinapril provide over 80% inhibition of plasma ACE for 24 hours. Inhibition of the pressor response to angiotensin I is shorter-lived, with a 20 mg dose giving 75% inhibition for about 4 hours, 50% inhibition for about 8 hours, and 20% inhibition at 24 hours. With chronic dosing, however, there is substantial inhibition of angiotensin II levels at 24 hours by doses of 20-80 mg.

Administration of 10 to 80 mg of quinapril to patients with mild to severe hypertension results in a reduction of sitting and standing blood pressure to about the same extent with minimal effect on heart rate. Symptomatic postural hypotension is infrequent although it can occur in patients who are salt-and/or volume-depleted (see WARNINGS). Antihypertensive activity commences within 1 hour with peak effects usually achieved by 2 to 4 hours after dosing. During chronic therapy, most of the blood pressure lowering effect of a given dose is obtained in 1-2 weeks. In multiple-dose studies, 10-80 mg per day in single or divided doses lowered systolic and diastolic blood pressure throughout the dosing interval, with a trough effect of about 5-11/3-7 mm Hg. The trough effect represents about 50% of the peak effect. While the dose-response relationship is relatively flat, doses of 40-80 mg were somewhat more effective at trough than 10-20 mg, and twice daily dosing tended to give a somewhat lower trough blood pressure than once daily dosing with the same total dose. The antihypertensive effect of quinapril continues during long-term therapy, with no evidence of loss of effectiveness.

Hemodynamic assessments in patients with hypertension indicate that blood pressure reduction produced by quinapril is accompanied by a reduction in total peripheral resistance and renal vascular resistance with little or no change in heart rate, cardiac index, renal blood flow, glomerular filtration rate, or filtration fraction.

Use of quinapril with a thiazide diuretic gives a blood-pressure lowering effect greater than that seen with either agent alone.

In patients with hypertension, quinapril 10-40 mg was similar in effectiveness to captopril, enalapril, propranolol, and thiazide diuretics.

Therapeutic effects appear to be the same for elderly (≥65 years of age) and younger adult patients given the same daily dosages, with no increase in adverse events in elderly patients.

INDICATIONS AND USAGE

Hypertension:

Quinapril tablets are indicated for the treatment of hypertension. It may be used alone or in combination with thiazide diuretics.

In using quinapril tablets, consideration should be given to the fact that another angiotensin-converting enzyme inhibitor, captopril, has caused agranulocytosis, particularly in patients with renal impairment or collagen vascular disease. Available data are insufficient to show that quinapril tablets does not have a similar risk (see WARNINGS).

Angioedema in black patients:

Black patients receiving ACE inhibitor monotherapy have been reported to have a higher incidence of angioedema compared to non-blacks. It should also be noted that in controlled clinical trials ACE inhibitors have an effect on blood pressure that is less in black patients than in non-blacks.

CONTRAINDICATIONS

Quinapril is contraindicated in patients who are hypersensitive to this product and in patients with a history of angioedema related to previous treatment with an ACE inhibitor.

WARNINGS

Anaphylactoid and Possibly Related Reactions:

Presumably because angiotensin-converting inhibitors affect the metabolism of eicosanoids and polypeptides, including endogenous bradykinin, patients receiving ACE inhibitors (including quinapril tablets) may be subject to a variety of adverse reactions, some of them serious.

Head and Neck Angioedema:

Angioedema of the face, extremities, lips, tongue, glottis, and larynx has been reported in patients treated with ACE inhibitors and has been seen in 0.1% of patients receiving quinapril.

In two similarly sized U.S. postmarketing trials that, combined, enrolled over 3,000 black patients and over 19,000 non-blacks, angioedema was reported in 0.30% and 0.55% of blacks (in study 1 and 2 respectively) and 0.39% and 0.17% of non-blacks.

Angioedema associated with laryngeal edema can be fatal. If laryngeal stridor or angioedema of the face, tongue, or glottis occurs, treatment with quinapril should be discontinued immediately, the patient treated in accordance with accepted medical care, and carefully observed until the swelling disappears. In instances where swelling is confined to the face and lips, the condition generally resolves without treatment; antihistamines may be useful in relieving symptoms. Where there is involvement of the tongue, glottis, or larynx likely to cause airway obstruction, emergency therapy including, but not limited to, subcutaneous epinephrine solution 1:1000 (0.3 to 0.5 mL) should be promptly administered (see ADVERSE REACTIONS).

Intestinal Angioedema:

Intestinal angioedema has been reported in patients treated with ACE inhibitors. These patients presented with abdominal pain (with or without nausea or vomiting); in some cases there was no prior history of facial angioedema and C-1 esterase levels were normal. The angioedema was diagnosed by procedures including abdominal CT scan or ultrasound, or at surgery, and symptoms resolved after stopping the ACE inhibitor. Intestinal angioedema should be included in the differential diagnosis of patients on ACE inhibitors presenting with abdominal pain.

Patients with a history of angioedema unrelated to ACE inhibitor therapy may be at increased risk of angioedema while receiving an ACE inhibitor (see also CONTRAINDICATIONS).

Anaphylactoid reactions during desensitization:

Two patients undergoing desensitizing treatment with hymenoptera venom while receiving ACE inhibitors sustained life-threatening anaphylactoid reactions. In the same patients, these reactions were avoided when ACE inhibitors were temporarily withheld, but they reappeared upon inadvertent rechallenge.

Anaphylactoid reactions during membrane exposure:

Anaphylactoid reactions have been reported in patients dialyzed with high-flux membranes and treated concomitantly with an ACE inhibitor. Anaphylactoid reactions have also been reported in patients undergoing low-density lipoprotein apheresis with dextran sulfate absorption.

Hepatic Failure:

Rarely, ACE inhibitors have been associated with a syndrome that starts with cholestatic jaundice and progresses to fulminant hepatic necrosis and (sometimes) death. The mechanism of this syndrome is not understood. Patients receiving ACE inhibitors who develop jaundice or marked elevations of hepatic enzymes should discontinue the ACE inhibitor and receive appropriate medical follow-up.

Hypotension:

Excessive hypotension is rare in patients with uncomplicated hypertension treated with quinapril alone. Patients with heart failure given quinapril commonly have some reduction in blood pressure, but discontinuation of therapy because of continuing symptomatic hypotension usually is not necessary when dosing instructions are followed. Caution should be observed when initiating therapy in patients with heart failure (see DOSAGE AND ADMINISTRATION). In controlled studies, syncope was observed in 0.4% of patients (N=3203); this incidence was similar to that observed for captopril (1%) and enalapril (0.8%).

Patients at risk of excessive hypotension, sometimes associated with oliguria and/or progressive azotemia, and rarely with acute renal failure and/or death, include patients with the following conditions or characteristics: hyponatremia, high dose diuretic therapy, recent intensive diuresis or increase in diuretic dose, renal dialysis, or severe volume and/or salt depletion of any etiology. It may be advisable to eliminate the diuretic (except in patients with heart failure), reduce the diuretic dose or cautiously increase salt intake (except in patients with heart failure) before initiating therapy with quinapril in patients at risk for excessive hypotension who are able to tolerate such adjustments.

In patients at risk of excessive hypotension, therapy with quinapril should be started under close medical supervision. Such patients should be followed closely for the first two weeks of treatment and whenever the dose of quinapril and/or diuretic is increased. Similar considerations may apply to patients with ischemic heart or cerebrovascular disease in whom an excessive fall in blood pressure could result in a myocardial infarction or a cerebrovascular accident.

If excessive hypotension occurs, the patient should be placed in the supine position and, if necessary, receive an intravenous infusion of normal saline. A transient hypotensive response is not a contraindication to further doses of quinapril, which usually can be given without difficulty once the blood pressure has stabilized. If symptomatic hypotension develops, a dose reduction or discontinuation of quinapril or concomitant diuretic may be necessary.

Neutropenia/Agranulocytosis:

Another ACE inhibitor, captopril, has been shown to cause agranulocytosis and bone marrow depression rarely in patients with uncomplicated hypertension, but more frequently in patients with renal impairment, especially if they also have a collagen vascular disease, such as systemic lupus erythematosus or scleroderma. Agranulocytosis did occur during quinapril treatment in one patient with a history of neutropenia during previous captopril therapy. Available data from clinical trials of quinapril are insufficient to show that, in patients without prior reactions to other ACE inhibitors, quinapril does not cause agranulocytosis at similar rates. As with other ACE inhibitors, periodic monitoring of white blood cell counts in patients with collagen vascular disease and/or renal disease should be considered.

Fetal/Neonatal Morbidity and Mortality:

ACE inhibitors can cause fetal and neonatal morbidity and death when administered to pregnant women. Several dozen cases have been reported in the world literature. When pregnancy is detected, ACE inhibitors should be discontinued as soon as possible.

The use of ACE inhibitors during the second and third trimesters of pregnancy has been associated with fetal and neonatal injury, including hypotension, neonatal skull hypoplasia, anuria, reversible or irreversible renal failure, and death. Oligohydramnios has also been reported, presumably resulting from decreased fetal renal function; oligohydramnios in this setting has been associated with fetal limb contractures, craniofacial deformation, and hypoplastic lung development. Prematurity, intrauterine growth retardation, and patent ductus arteriosus have also been reported, although it is not clear whether these occurrences were due to the ACE inhibitor exposure.

These adverse effects do not appear to have resulted from intrauterine ACE inhibitor exposure that has been limited to the first trimester. Mothers whose embryos and fetuses are exposed to ACE inhibitors only during the first trimester should be so informed. Nonetheless, when patients become pregnant, physicians should make every effort to discontinue the use of quinapril as soon as possible.

Rarely (probably less often than once in every thousand pregnancies), no alternative to ACE inhibitors will be found. In these rare cases, the mothers should be apprised of the potential hazards to their fetuses, and serial ultrasound examinations should be performed to assess the intraamniotic environment.

If oligohydramnios is observed, quinapril should be discontinued unless it is considered lifesaving for the mother. Contraction stress testing (CST), a non-stress test (NST), or biophysical profiling (BPP) may be appropriate, depending upon the week of pregnancy. Patients and physicians should be aware, however, that oligohydramnios may not appear until after the fetus has sustained irreversible injury.

Infants with histories of in utero exposure to ACE inhibitors should be closely observed for hypotension, oliguria, and hyperkalemia. If oliguria occurs, attention should be directed toward support of blood pressure and renal perfusion. Exchange transfusion or dialysis may be required as a means of reversing hypotension and/or substituting for disordered renal function. Removal of quinapril, which crosses the placenta, from the neonatal circulation is not significantly accelerated by these means.

No teratogenic effects of quinapril were seen in studies of pregnant rats and rabbits. On a mg/kg basis, the doses used were up to 180 times (in rats) and one time (in rabbits) the maximum recommended human dose.

PRECAUTIONS

General:

Impaired renal function:

As a consequence of inhibiting the renin-angiotensin-aldosterone system, changes in renal function may be anticipated in susceptible individuals. In patients with severe heart failure whose renal function may depend on the activity of the renin- angiotensin-aldosterone system, treatment with ACE inhibitors, including quinapril, may be associated with oliguria and/or progressive azotemia and rarely acute renal failure and/or death.

In clinical studies in hypertensive patients with unilateral or bilateral renal artery stenosis, increases in blood urea nitrogen and serum creatinine have been observed in some patients following ACE inhibitor therapy. These increases were almost always reversible upon discontinuation of the ACE inhibitor and/or diuretic therapy. In such patients, renal function should be monitored during the first few weeks of therapy.

Some patients with hypertension or heart failure with no apparent preexisting renal vascular disease have developed increases in blood urea and serum creatinine, usually minor and transient, especially when quinapril has been given concomitantly with a diuretic. This is more likely to occur in patients with preexisting renal impairment. Dosage reduction and/or discontinuation of any diuretic and/or quinapril may be required.

Evaluation of patients with hypertension should always include assessment of renal function (see DOSAGE AND ADMINISTRATION).

Hyperkalemia and potassium-sparing diuretics:

In clinical trials, hyperkalemia (serum potassium ≥5.8 mmol/L) occurred in approximately 2% of patients receiving quinapril. In most cases, elevated serum potassium levels were isolated values which resolved despite continued therapy. Less than 0.1% of patients discontinued therapy due to hyperkalemia. Risk factors for the development of hyperkalemia include renal insufficiency, diabetes mellitus, and the concomitant use of potassium-sparing diuretics, potassium supplements, and/or potassium-containing salt substitutes, which should be used cautiously, if at all, with quinapril (see PRECAUTIONS, Drug Interactions).

Cough:

Presumably due to the inhibition of the degradation of endogenous bradykinin, persistent non-productive cough has been reported with all ACE inhibitors, always resolving after discontinuation of therapy. ACE inhibitor-induced cough should be considered in the differential diagnosis of cough.

Surgery/anesthesia:

In patients undergoing major surgery or during anesthesia with agents that produce hypotension, quinapril will block angiotensin II formation secondary to compensatory renin release. If hypotension occurs and is considered to be due to this mechanism, it can be corrected by volume expansion.

Information for Patients:

Pregnancy:

Female patients of childbearing age should be told about the consequences of second- and third-trimester exposure to ACE inhibitors, and they should also be told that these consequences do not appear to have resulted from intrauterine ACE-inhibitor exposure that has been limited to the first trimester. These patients should be asked to report pregnancies to their physicians as soon as possible.

Angioedema:

Angioedema, including laryngeal edema can occur with treatment with ACE inhibitors, especially following the first dose. Patients should be so advised and told to report immediately any signs or symptoms suggesting angioedema (swelling of face, extremities, eyes, lips, tongue, difficulty in swallowing or breathing) and to stop taking the drug until they have consulted with their physician (see WARNINGS).

Symptomatic hypotension:

Patients should be cautioned that lightheadedness can occur, especially during the first few days of quinapril therapy, and that it should be reported to a physician. If actual syncope occurs, patients should be told to not take the drug until they have consulted with their physician (see WARNINGS).

All patients should be cautioned that inadequate fluid intake or excessive perspiration, diarrhea, or vomiting can lead to an excessive fall in blood pressure because of reduction in fluid volume, with the same consequences of lightheadedness and possible syncope.

Patients planning to undergo any surgery and/or anesthesia should be told to inform their physician that they are taking an ACE inhibitor.

Hyperkalemia:

Patients should be told not to use potassium supplements or salt substitutes containing potassium without consulting their physician (see PRECAUTIONS).

Neutropenia:

Patients should be told to report promptly any indication of infection (eg, sore throat, fever) which could be a sign of neutropenia.

NOTE: As with many other drugs, certain advice to patients being treated with quinapril is warranted. This information is intended to aid in the safe and effective use of this medication. It is not a disclosure of all possible adverse or intended effects.

Drug Interactions:

Concomitant diuretic therapy:

As with other ACE inhibitors, patients on diuretics, especially those on recently instituted diuretic therapy, may occasionally experience an excessive reduction of blood pressure after initiation of therapy with quinapril. The possibility of hypotensive effects with quinapril may be minimized by either discontinuing the diuretic or cautiously increasing salt intake prior to initiation of treatment with quinapril. If it is not possible to discontinue the diuretic, the starting dose of quinapril should be reduced (see DOSAGE AND ADMINISTRATION).

Agents increasing serum potassium:

Quinapril can attenuate potassium loss caused by thiazide diuretics and increase serum potassium when used alone. If concomitant therapy of quinapril with potassium-sparing diuretics (eg, spironolactone, triamterene, or amiloride), potassium supplements, or potassium-containing salt substitutes is indicated, they should be used with caution along with appropriate monitoring of serum potassium (see PRECAUTIONS).

Tetracycline and other drugs that interact with magnesium:

Simultaneous administration of tetracycline with quinapril reduced the absorption of tetracycline by approximately 28% to 37%, possibly due to the high magnesium content in quinapril tablets. This interaction should be considered if coprescribing quinapril and tetracycline or other drugs that interact with magnesium.

Lithium:

Increased serum lithium levels and symptoms of lithium toxicity have been reported in patients receiving concomitant lithium and ACE inhibitor therapy. These drugs should be coadministered with caution and frequent monitoring of serum lithium levels is recommended. If a diuretic is also used, it may increase the risk of lithium toxicity.

Gold:

Nitritoid reactions (symptoms include facial flushing, nausea, vomiting, and hypotension) have been reported rarely in patients on therapy with injectable gold (sodium aurothiomalate) and concomitant ACE inhibitor therapy.

Other agents:

Drug interaction studies of quinapril with other agents showed:

- Multiple dose therapy with propranolol or cimetidine has no effect on the pharmacokinetics of single doses of quinapril.
- The anticoagulant effect of a single dose of warfarin (measured by prothrombin time) was not significantly changed by quinapril coadministration twice-daily.
- Quinapril treatment did not affect the pharmacokinetics of digoxin.
- No pharmacokinetic interaction was observed when single doses of quinapril and hydrochlorothiazide were administered concomitantly.
- Co-administration of multiple 10 mg doses of atorvastatin with 80 mg of quinapril resulted in no significant change in the steady-state pharmacokinetic parameters of atorvastatin.

Carcinogenesis, Mutagenesis, Impairment of Fertility:

Quinapril hydrochloride was not carcinogenic in mice or rats when given in doses up to 75 or 100 mg/kg/day (50 to 60 times the maximum human daily dose, respectively, on an mg/kg basis and 3.8 to 10 times the maximum human daily dose when based on an mg/m^2 basis) for 104 weeks. Female rats given the highest dose level had an increased incidence of mesenteric lymph node hemangiomas and skin/subcutaneous lipomas. Neither quinapril nor quinaprilat were mutagenic in the Ames bacterial assay with or without metabolic activation. Quinapril was also negative in the following genetic toxicology studies: in vitro mammalian cell point mutation, sister chromatid exchange in cultured mammalian cells, micronucleus test with mice, in vitro chromosome aberration with V79 cultured lung cells, and in an in vivo cytogenetic study with rat bone marrow. There were no adverse effects on fertility or reproduction in rats at doses up to 100 mg/kg/day (60 and 10 times the maximum daily human dose when based on mg/kg and mg/m^2, respectively).

Pregnancy:

Pregnancy Categories C (first trimester) and D (second and third trimesters): See WARNINGS, Fetal/Neonatal Morbidity and Mortality.

Nursing Mothers:

Because quinapril is secreted in human milk, caution should be exercised when this drug is administered to a nursing woman.

Pediatric Use:

The safety and effectiveness of quinapril in pediatric patients have not been established.

Geriatric Use:

Clinical studies of quinapril did not include sufficient numbers of subjects aged 65 and over to determine whether they respond differently from younger subjects. Other reported clinical experience has not identified differences in responses between the elderly and younger patients.

In general, dose selection for an elderly patient should be cautious, usually starting at the low end of the dosing range, reflecting the greater frequency of decreased hepatic, renal or cardiac function, and of concomitant disease or other drug therapy.

This drug is known to be substantially excreted by the kidney, and the risk of toxic reactions to this drug may be greater in patients with impaired renal function. Because elderly patients are more likely to have decreased renal function, care should be taken in dose selection, and it may be useful to monitor renal function.

Elderly patients exhibited increased area under the plasma concentration time curve and peak levels for quinaprilat compared to values observed in younger patients; this appeared to relate to decreased renal function rather than to age itself.

ADVERSE REACTIONS

Hypertension:

Quinapril has been evaluated for safety in 4960 subjects and patients. Of these, 3203 patients, including 655 elderly patients, participated in controlled clinical trials. Quinapril has been evaluated for long-term safety in over 1400 patients treated for 1 year or more.

Adverse experiences were usually mild and transient.

In placebo-controlled trials, discontinuation of therapy because of adverse events was required in 4.7% of patients with hypertension.

Adverse experiences probably or possibly related to therapy or of unknown relationship to therapy occurring in 1% or more of the 1563 patients in placebo-controlled hypertension trials who were treated with quinapril hydrochloride are shown below.

Adverse Events in Placebo-Controlled Trials
 | Quinapril Hydrochloride; (N=1563); Incidence; (Discontinuance) | Placebo; (N=579); Incidence; (Discontinuance)
Headache | 5.6 (0.7) | 10.9 (0.7)
Dizziness | 3.9 (0.8) | 2.6 (0.2)
Fatigue | 2.6 (0.3) | 1.0
Coughing | 2.0 (0.5) | 0.0
Nausea and/or Vomiting | 1.4 (0.3) | 1.9 (0.2)
Abdominal Pain | 1.0 (0.2) | 0.7

Hypertension:

Clinical adverse experiences probably, possibly, or definitely related, or of uncertain relationship to therapy occurring in 0.5% to 1.0% (except as noted) of the patients with hypertension treated with quinapril hydrochloride (with or without concomitant diuretic) in controlled or uncontrolled trials (N=4847) and less frequent, clinically significant events seen in clinical trials or post-marketing experience (the rarer events are in italics) include (listed by body system):

General:

Back pain, malaise, viral infections, anaphylactoid reaction

Cardiovascular:

Palpitation, vasodilation, tachycardia, heart failure, hyperkalemia, myocardial infarction, cerebrovascular accident, hypertensive crisis, angina pectoris, orthostatic hypotension, cardiac rhythm disturbances, cardiogenic shock

Hematology:

Hemolytic anemia

Gastrointestinal:

Flatulence, dry mouth or throat, constipation, gastrointestinal hemorrhage, pancreatitis, abnormal liver function tests, dyspepsia

Nervous/Psychiatric:

Somnolence, vertigo, syncope, nervousness, depression, insomnia, paresthesia

Integumentary:

Alopecia, increased sweating, pemphigus, pruritus, exfoliative dermatitis, photosensitivity reaction, dermatopolymyositis

Urogenital:

Urinary tract infection, impotence, acute renal failure, worsening renal failure

Respiratory:

Eosinophilic pneumonitis

Other:

Amblyopia, edema, arthralgia, pharyngitis, agranulocytosis, hepatitis, thrombocytopenia

Fetal/Neonatal Morbidity and Mortality:

See WARNINGS, Fetal/Neonatal Morbidity and Mortality.

Angioedema:

Angioedema has been reported in patients receiving quinapril (0.1%). Angioedema associated with laryngeal edema may be fatal. If angioedema of the face, extremities, lips, tongue, glottis, and/or larynx occurs, treatment with quinapril should be discontinued and appropriate therapy instituted immediately. (See WARNINGS).

Clinical Laboratory Test Findings:

Hematology:

(See WARNINGS).

Hyperkalemia:

(See PRECAUTIONS).

Creatinine and Blood Urea Nitrogen:

Increases (>1.25 times the upper limit of normal) in serum creatinine and blood urea nitrogen were observed in 2% and 2%, respectively, of all patients treated with quinapril alone. Increases are more likely to occur in patients receiving concomitant diuretic therapy than in those on quinapril alone. These increases often remit on continued therapy.

OVERDOSAGE

Doses of 1440 to 4280 mg/kg of quinapril cause significant lethality in mice and rats.

No specific information is available on the treatment of overdosage with quinapril. The most likely clinical manifestation would be symptoms attributable to severe hypotension.

Laboratory determinations of serum levels of quinapril and its metabolites are not widely available, and such determinations have, in any event, no established role in the management of quinapril overdose.

No data are available to suggest physiological maneuvers (eg, maneuvers to change pH of the urine) that might accelerate elimination of quinapril and its metabolites.

Hemodialysis and peritoneal dialysis have little effect on the elimination of quinapril and quinaprilat. Angiotensin II could presumably serve as a specific antagonist-antidote in the setting of quinapril overdose, but angiotensin II is essentially unavailable outside of scattered research facilities. Because the hypotensive effect of quinapril is achieved through vasodilation and effective hypovolemia, it is reasonable to treat quinapril overdose by infusion of normal saline solution.

DOSAGE AND ADMINISTRATION

Hypertension:

Monotherapy:

The recommended initial dosage of quinapril tablets in patients not on diuretics is 10 or 20 mg once daily. Dosage should be adjusted according to blood pressure response measured at peak (2-6 hours after dosing) and trough (predosing). Generally, dosage adjustments should be made at intervals of at least 2 weeks. Most patients have required dosages of 20, 40, or 80 mg/day, given as a single dose or in two equally divided doses. In some patients treated once daily, the antihypertensive effect may diminish toward the end of the dosing interval. In such patients an increase in dosage or twice daily administration may be warranted. In general, doses of 40-80 mg and divided doses give a somewhat greater effect at the end of the dosing interval.

Concomitant Diuretics:

If blood pressure is not adequately controlled with quinapril tablets monotherapy, a diuretic may be added. In patients who are currently being treated with a diuretic, symptomatic hypotension occasionally can occur following the initial dose of quinapril tablets. To reduce the likelihood of hypotension, the diuretic should, if possible, be discontinued 2 to 3 days prior to beginning therapy with quinapril tablets (see WARNINGS). Then, if blood pressure is not controlled with quinapril tablets alone, diuretic therapy should be resumed.

If the diuretic cannot be discontinued, an initial dose of 5 mg quinapril tablets should be used with careful medical supervision for several hours and until blood pressure has stabilized.

The dosage should subsequently be titrated (as described above) to the optimal response (see WARNINGS, PRECAUTIONS, and Drug Interactions).

Renal Impairment:

Kinetic data indicate that the apparent elimination half-life of quinaprilat increases as creatinine clearance decreases. Recommended starting doses, based on clinical and pharmacokinetic data from patients with renal impairment, are as follows:

Creatinine; Clearance | Maximum Recommended; Initial Dose
>60 mL/min | 10 mg
30-60 mL/min | 5 mg
10-30 mL/min | 2.5 mg
<10 mL/min | Insufficient data for; dosage recommendation

Patients should subsequently have their dosage titrated (as described above) to the optimal response.

Elderly (≥65 years):

The recommended initial dosage of quinapril tablets in elderly patients is 10 mg given once daily followed by titration (as described above) to the optimal response.

Following the initial dose of quinapril tablets, the patient should be observed under medical supervision for at least two hours for the presence of hypotension or orthostasis and, if present, until blood pressure stabilizes. The appearance of hypotension, orthostasis, or azotemia early in dose titration should not preclude further careful dose titration. Consideration should be given to reducing the dose of concomitant diuretics.

DOSE ADJUSTMENTS IN PATIENTS WITH HEART FAILURE AND RENAL IMPAIRMENT OR HYPONATREMIA

Pharmacokinetic data indicate that quinapril elimination is dependent on level of renal function. In patients with heart failure and renal impairment, the recommended initial dose of quinapril is 5 mg in patients with a creatinine clearance above 30 mL/min and 2.5 mg in patients with a creatinine clearance of 10 to 30 mL/min. There is insufficient data for dosage recommendation in patients, with a creatinine clearance less than 10 mL/min. (See WARNINGS, and PRECAUTIONS, Drug Interactions).

If the initial dose is well tolerated, quinapril may be administered the following day as a twice daily regimen. In the absence of excessive hypotension or significant deterioration of renal function, the dose may be increased at weekly intervals based on clinical and hemodynamic response.

HOW SUPPLIED

Quinapril tablets are supplied as follows:

5-mg tablets: Yellow colored, oval shaped, film-coated tablets, debossed with ‘L’ & ‘U’ on either side of the breakline on one side and ‘F01’ on the other side.

NDC 21695-393-30 bottles of 30 tablets

10-mg tablets: Yellow colored, circular shaped, film-coated tablets, debossed with ‘LU’ on one side and ‘F02’ on the other side.

NDC 21695-394-30 bottles of 30 tablets

Dispense in well-closed containers as defined in the USP.

Storage: Store at 20°to 25°C (68°to 77°F) [See USP Controlled Room Temperature]. Protect from light.

Manufactured for:
Lupin Pharmaceuticals, Inc.
Baltimore, Maryland 21202
United States

Manufactured by:
Lupin Limited
Goa 403 722
INDIA

Revised: September 2010 ID#:222888

Repackaged by:

Rebel Distributors Corp

Thousand Oaks, CA 91320